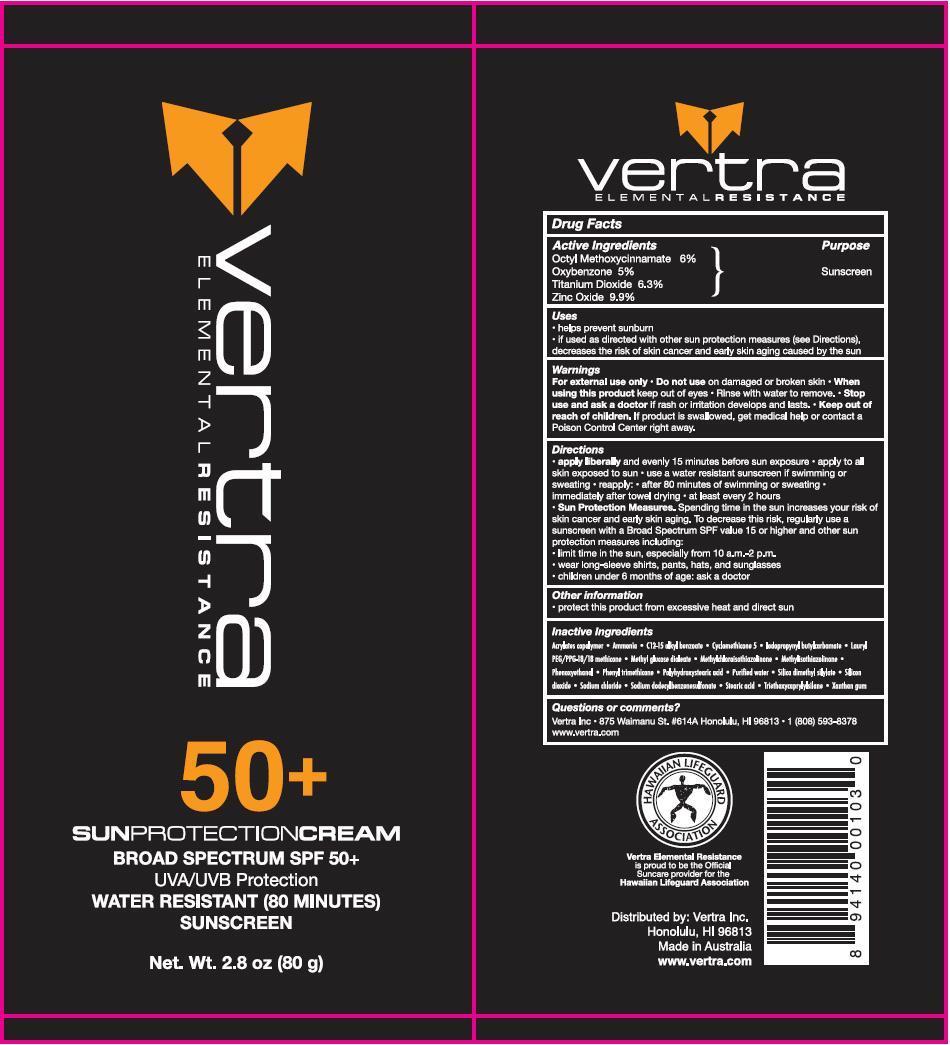 DRUG LABEL: Vertra Elemental Resistance
NDC: 69750-001 | Form: LOTION
Manufacturer: Vertra (Aust) Pty Ltd
Category: otc | Type: HUMAN OTC DRUG LABEL
Date: 20150518

ACTIVE INGREDIENTS: OCTINOXATE 4.8 g/80 g; OXYBENZONE 4 g/80 g; TITANIUM DIOXIDE 5 g/80 g; ZINC OXIDE 7.9 g/80 g
INACTIVE INGREDIENTS: AMMONIA; ALKYL (C12-15) BENZOATE; CYCLOMETHICONE 5; IODOPROPYNYL BUTYLCARBAMATE; LAURYL PEG/PPG-18/18 METHICONE; METHYL GLUCOSE DIOLEATE; METHYLCHLOROISOTHIAZOLINONE; METHYLISOTHIAZOLINONE; PHENOXYETHANOL; PHENYL TRIMETHICONE; POLYHYDROXYSTEARIC ACID (2300 MW); WATER; SILICA DIMETHYL SILYLATE; SILICON DIOXIDE; SODIUM CHLORIDE; SODIUM DODECYLBENZENESULFONATE; STEARIC ACID; TRIETHOXYCAPRYLYLSILANE; XANTHAN GUM

Drug Facts

Active Ingredients

Octyl Methoxycinnamate 6%
Oxybenzone 5%
Titanium Dioxide 6.3%
Zinc Oxide 9.9%

Purpose

Sunscreen

Uses

- helps prevent sunburn
- if used as directed with other sun protection measures (see Directions), decreases the risk of skin cancer and early skin aging caused by the sun

Warnings

For external use only

Do not use on damaged or broken skin

When using this product keep out of eyes - Rinse with water to remove.

Stop use and ask a doctor if rash or irritation develops and lasts.

Keep out of reach of children. If product is swallowed, get medical help or contact a Poison Control Center right away.

Directions

- apply liberally and evenly 15 minutes before sun exposure
- apply to all skin exposed to sun
- use a water resistant sunscreen if swimming or sweating
- reapply after 80 minutes of swimming or sweating, immediately after towel drying, at least every 2 hours
- Sun Protection Measures. Spending time in the sun increases your risk of skin cancer and early skin aging. to decrease this risk, regularly use a sunscreen with a Broad Spectrum SPF value 15 or higher and other sun protection measures including: limit time in the sun, especially from 10a.m.-2p.m., wear long-sleeve shirts, pants, hats, and sunglasses, children under 6 months of age: ask a doctor

Other information

- protect this product from excessive heat and direct sun

Inactive Ingredients

Acrylates copolymer, Ammonia, C12-15 alkyl benzoate, Cyclomethicone 5, Iodopropynl butylcarbamate, Lauryl PEG/PPG-18/18 methicone, Methyl glucose dioleate, Methlchloroisothiazolinone, Methylisothiazolinone, Phenoxyethanol, Phenyl trimethicone, Polyhydroxystearic acid, Purified water, Silica dimethyl silylate, Silicone dioxide, Sodium chloride, Sodium dodecylbenzenesulfonate, Stearic acid, Triethoxycaprylylsilane, Xanthan gum

Questions or comments?

Vertra Inc - 875 Waimanu St. #614A Honolulu, HI 96813 - 1(808)593-8378 www.vertra.com

DESCRIPTION

Vertra Elemental Resistance is proud to be the Official Suncare provider for the Hawaiian Lifeguard Association

Distributed by: Vertra Inc. Honolulu, HI 96813
Made in Australia
www.vertra.com

Principal Display Panel

Vertra Elemental Resistance

50+ SUNPROTECTIONCREAM
BROAD SPECTRUM SPF50+
UVA/UVB Protection
WATER RESISTANT (80 MINUTES) SUNSCREEN

Net. Wt. 2.8 oz (80 g)